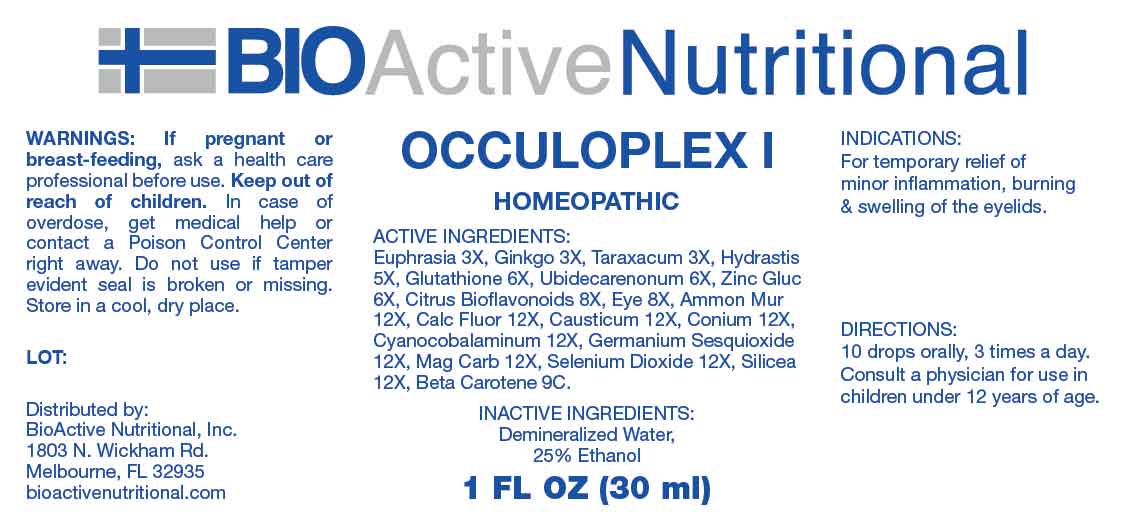 DRUG LABEL: Occuloplex
NDC: 43857-0600 | Form: LIQUID
Manufacturer: BioActive Nutritional, Inc.
Category: homeopathic | Type: HUMAN OTC DRUG LABEL
Date: 20240508

ACTIVE INGREDIENTS: EUPHRASIA STRICTA 3 [hp_X]/1 mL; GINKGO 3 [hp_X]/1 mL; TARAXACUM OFFICINALE 3 [hp_X]/1 mL; GOLDENSEAL 5 [hp_X]/1 mL; GLUTATHIONE 6 [hp_X]/1 mL; UBIDECARENONE 6 [hp_X]/1 mL; ZINC GLUCONATE 6 [hp_X]/1 mL; CITRUS BIOFLAVONOIDS 8 [hp_X]/1 mL; SUS SCROFA EYE 8 [hp_X]/1 mL; AMMONIUM CHLORIDE 12 [hp_X]/1 mL; CALCIUM FLUORIDE 12 [hp_X]/1 mL; CAUSTICUM 12 [hp_X]/1 mL; CONIUM MACULATUM FLOWERING TOP 12 [hp_X]/1 mL; CYANOCOBALAMIN 12 [hp_X]/1 mL; GERMANIUM SESQUIOXIDE 12 [hp_X]/1 mL; MAGNESIUM CARBONATE 12 [hp_X]/1 mL; SELENIUM DIOXIDE 12 [hp_X]/1 mL; SILICON DIOXIDE 12 [hp_X]/1 mL; BETA CAROTENE 9 [hp_C]/1 mL
INACTIVE INGREDIENTS: WATER; ALCOHOL

DRUG FACTS:

ACTIVE INGREDIENTS:

Euphrasia Officinalis 3X, Ginkgo Biloba 3X, Taraxacum Officinale 3X, Hydrastis Canadensis 5X, Glutathione 6X, Ubidecarenonum 6X, Zincum Gluconicum 6X, Citrus Bioflavonoids 8X, Eye 8X, Ammonium Muriaticum 12X, Calcarea Fluorica 12X, Causticum 12X, Conium Maculatum 12X, Cyanocobalaminum 12X, Germanium Sesquioxide 12X, Magnesia Carbonica 12X, Selenium Dioxide 12X, Silicea 12X, Beta Carotene 9C.

INDICATIONS:

For temporary relief of minor inflammation, burning & swelling of the eyelids.

WARNINGS:

If pregnant or breast-feeding, ask a health care professional before use.

Keep out of reach of children. In case of overdose, get medical help or contact a Poison Control Center right away.

Do not use if tamper evident seal is broken or missing.

Store in cool, dry place.

KEEP OUT OF REACH OF CHILDREN:

In case of overdose, get medical help or contact a Poison Control Center right away.

DIRECTIONS:

10 drops orally, 3 times a day. Consult a physician for use in children under 12 years of age.

INDICATIONS:

For temporary relief of minor inflammation, burning & swelling of the eyelids.

INACTIVE INGREDIENTS:

Demineralized Water, 25% Ethanol

QUESTIONS:

Distributed by:

BioActive Nutritional, Inc.

1803 N. Wickham Rd.

Melbourne, FL 32935

bioactivenutritional.com

PACKAGE LABEL DISPLAY:

BIOActive Nutritional

OCCULOPLEX I

HOMEOPATHIC

1 FL OZ (30 ml)